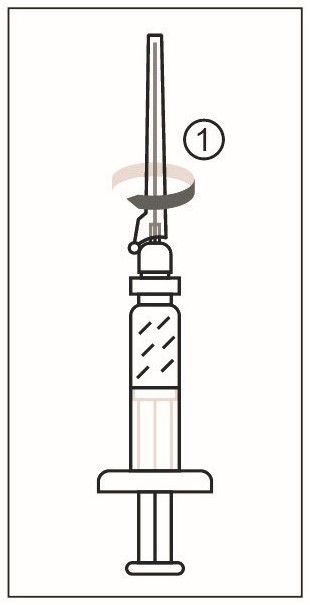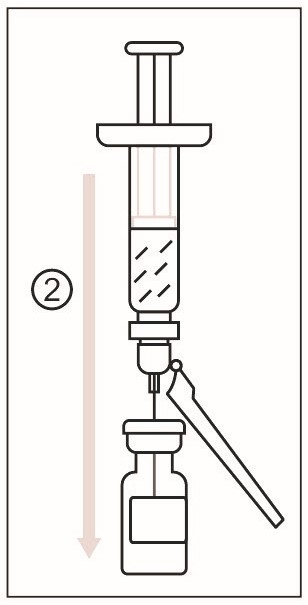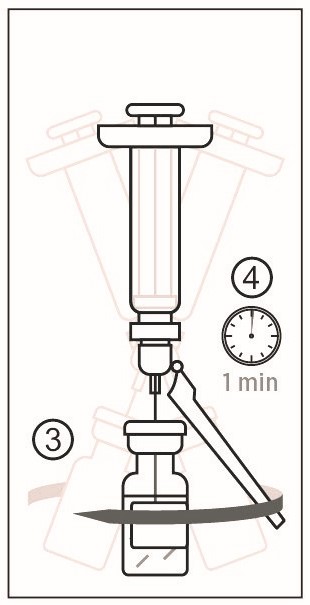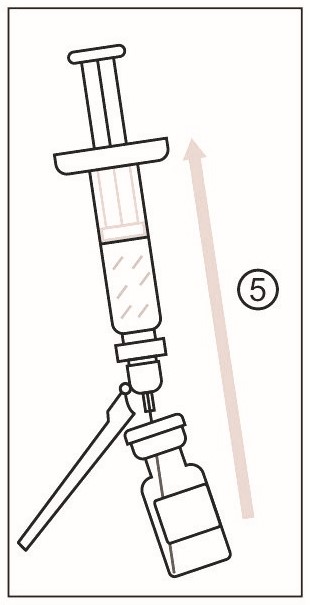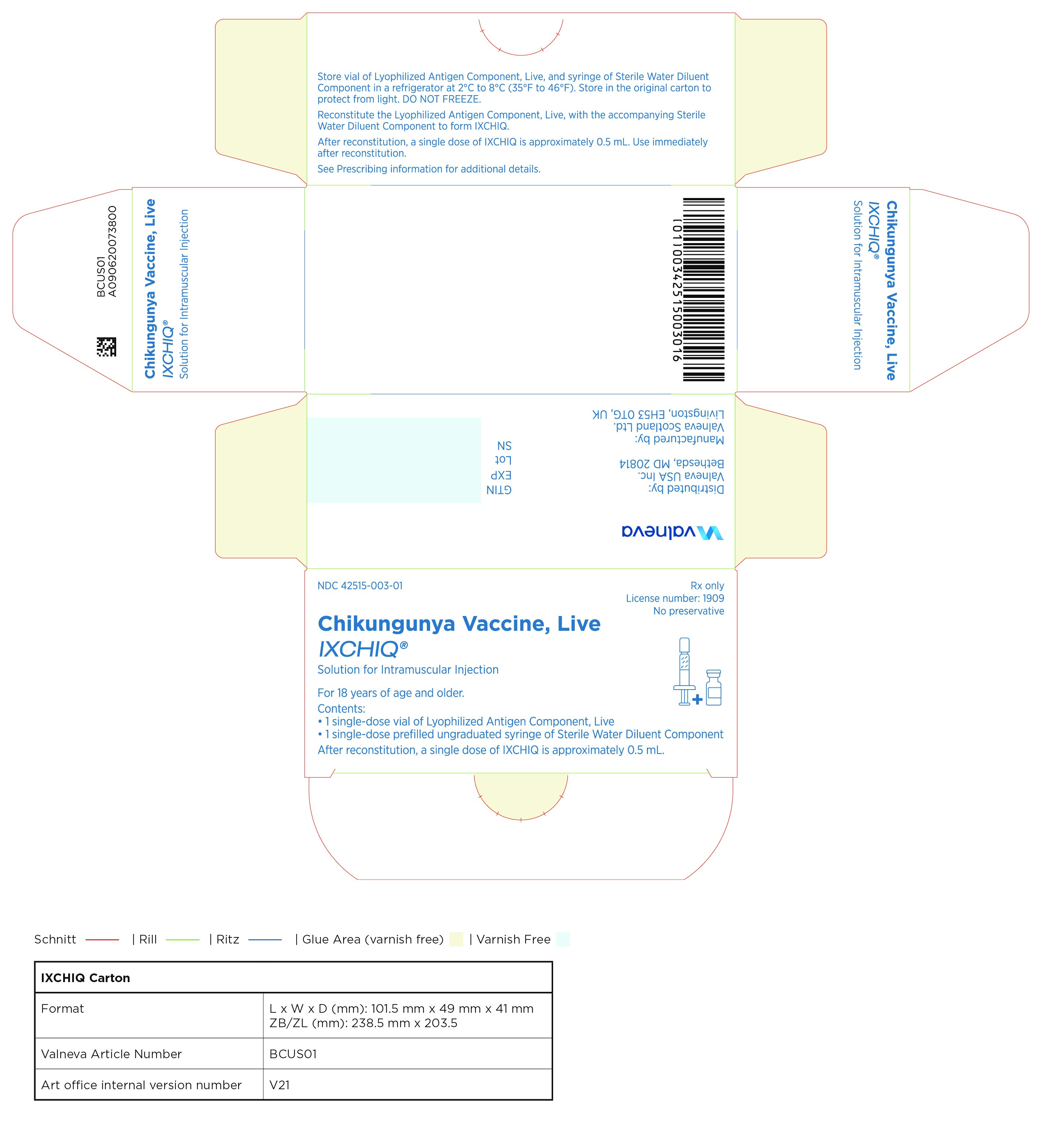 DRUG LABEL: IXCHIQ
NDC: 42515-003 | Form: INJECTION, POWDER, LYOPHILIZED, FOR SOLUTION
Manufacturer: Valneva Scotland Ltd.
Category: other | Type: VACCINE LABEL
Date: 20231109

ACTIVE INGREDIENTS: CHIKUNGUNYA VIRUS LR2006 OPY1 (ATTENUATED STRAIN) ANTIGEN 3 [TCID_50]/0.5 mL

HIGHLIGHTS OF PRESCRIBING INFORMATION

IXCHIQ
These highlights do not include all the information needed to use IXCHIQ. See full prescribing information for IXCHIQ.
Initial U.S. Approval: 2023

1 INDICATIONS AND USAGE

IXCHIQ is a vaccine indicated for the prevention of disease caused by chikungunya virus (CHIKV) in individuals 18 years of age and older who are at increased risk of exposure to CHIKV. (1)

This indication is approved under accelerated approval based on anti-CHIKV neutralizing antibody titers. Continued approval for this indication may be contingent upon verification and description of clinical benefit in confirmatory studies.

2 DOSAGE AND ADMINISTRATION

For intramuscular use only.

Administer IXCHIQ as a single approximately 0.5 mL dose. (2.3)

3 DOSAGE FORMS AND STRENGTHS

IXCHIQ is a solution for injection. After reconstitution, a single dose is approximately 0.5 mL. (3)

4 CONTRAINDICATIONS

- Immunocompromised individuals. (4.1)
- Individuals with a history of a severe allergic reaction (e.g., anaphylaxis) to any component of IXCHIQ. (4.2)

5 WARNINGS AND PRECAUTIONS

- IXCHIQ may cause severe or prolonged chikungunya-like adverse reactions. (5.2)
- Vertical transmission of wild-type CHIKV from pregnant individuals with viremia at delivery is common and can cause potentially fatal CHIKV disease in neonates. Vaccine viremia occurs in the first week following administration of IXCHIQ, with resolution of viremia by 14 days after vaccination. It is not known if the vaccine virus can be vertically transmitted and cause fetal or neonatal adverse reactions. (5.3)
- Syncope (fainting) may occur in association with administration of injectable vaccines, including IXCHIQ. Procedures should be in place to avoid injury from fainting. (5.4)

6 ADVERSE REACTIONS

In clinical studies, the most common solicited injection site reaction (>10%) was tenderness (10.6%). The most common solicited systemic adverse reactions (>10%) were headache (31.6%), fatigue (28.5%), myalgia (23.9%), arthralgia (17.2%), fever (13.5%) and nausea (11.2%). (6.1)

To report SUSPECTED ADVERSE REACTIONS, contact Valneva USA Inc. at 1-844-349-4276 or VAERS at 1-800-822-7967 or http://vaers.hhs.gov.

8 USE IN SPECIFIC POPULATIONS

A decision to administer IXCHIQ during pregnancy should take into consideration the individual’s risk of wild-type CHIKV infection, gestational age, and risks to the fetus or neonate from vertical transmission of wild-type CHIKV. (8.1)

FULL PRESCRIBING INFORMATION

1 INDICATIONS AND USAGE

IXCHIQ is a vaccine indicated for the prevention of disease caused by chikungunya virus (CHIKV) in individuals 18 years of age and older who are at increased risk of exposure to CHIKV.

This indication is approved under accelerated approval based on anti-CHIKV neutralizing antibody levels [See Clinical Studies (14)]. Continued approval for this indication may be contingent upon verification and description of clinical benefit in confirmatory studies.

2 DOSAGE AND ADMINISTRATION

For intramuscular injection only.

2.1 Recommended Dose and Schedule

After reconstitution, a single dose of IXCHIQ is approximately 0.5 mL.

Administer a single dose of IXCHIQ by intramuscular injection.

2.2 Preparation for Administration

Reconstitute the Lyophilized Antigen Component, Live (a white to slightly yellowish powder) only with the accompanying Sterile Water Diluent Component to form IXCHIQ. The reconstituted vaccine is a clear, colorless to slightly yellowish liquid solution. Parenteral drug products should be inspected visually for particulate matter and discoloration prior to administration, whenever solution and container permit. If either of these conditions exists, do not administer the vaccine.

DOSAGE AND ADMINISTRATION

Figure 1

1) Remove the cap from the syringe of Sterile Water Diluent Component. Attach a needle to the Luer lock of the syringe.

DOSAGE AND ADMINISTRATION

Figure 2

2) Cleanse the stopper of the vial of Lyophilized Antigen Component, Live. Slowly transfer the entire contents of the prefilled syringe of Sterile Water Diluent Component into the vial.

DOSAGE AND ADMINISTRATION

Figure 3

3) Gently swirl the vial to dissolve the Lyophilized Antigen Component, Live. Do not shake or invert the vial.
4) After swirling, wait for at least one minute for complete reconstitution of the vaccine.

DOSAGE AND ADMINISTRATION

Figure 4

5) After reconstitution, slightly tilt the vial and withdraw the entire contents into the syringe. Do not invert the vial.

2.3 Administration

After reconstitution, immediately administer IXCHIQ intramuscularly.

3 DOSAGE FORMS AND STRENGTHS

IXCHIQ is a solution for injection. After reconstitution, a single dose is approximately 0.5 mL.

4 CONTRAINDICATIONS

4.1 Immunocompromised Individuals

Do not administer IXCHIQ to individuals who are immunodeficient or immunosuppressed due to disease or medical therapy (e.g., from hematologic and solid tumors, receipt of chemotherapy, congenital immunodeficiency, long-term immunosuppressive therapy or patients with HIV infection who are severely immunocompromised).

4.2 Severe Allergic Reactions

Do not administer IXCHIQ to individuals with a history of a severe allergic reaction (e.g., anaphylaxis) to any component of the vaccine [see Description (11)].

5 WARNINGS AND PRECAUTIONS

5.1 Management of Acute Allergic Reactions

Appropriate medical treatment used to manage immediate allergic reactions must be available in the event an acute anaphylactic reaction occurs following administration of IXCHIQ.

5.2 Risk of Severe or Prolonged Chikungunya-like Adverse Reactions

Vaccination with IXCHIQ may cause severe or prolonged chikungunya-like adverse reactions. Severe chikungunya-like adverse reactions that prevented daily activity and/or required medical intervention occurred in 1.6% of 3,082 IXCHIQ recipients and no placebo recipients. Two IXCHIQ recipients required hospitalization for severe myalgia and for hypovolemic hyponatremia and atrial fibrillation, respectively. Fourteen IXCHIQ recipients had prolonged (duration at least 30 days) chikungunya-like adverse reactions [See Adverse Reactions (6.1)].

5.3 Potential for Vertical Transmission of Vaccine Virus and Fetal/Neonatal Adverse Reactions

Vertical transmission of wild-type CHIKV to neonates from pregnant individuals with viremia at delivery is common and can cause severe, potentially fatal CHIKV disease in neonates. Vertical transmission of wild-type CHIKV and fetal death attributable to CHIKV in the context of antepartum infection has been reported to occur infrequently [See Use in Specific Populations (8.1)].

Vaccine viremia occurs in the first week following administration of IXCHIQ, with resolution of viremia by 14 days after vaccination [See Clinical Pharmacology (12.2)]. It is not known if the vaccine virus can be transmitted from a pregnant individual to the fetus or neonate and cause fetal or neonatal adverse reactions.

Decisions to administer IXCHIQ during pregnancy should take into consideration the individual’s risk of exposure to wild-type CHIKV, gestational age, and risks to the fetus or neonate from vertical transmission of wild-type CHIKV.

Closely monitor neonates for 7 days after birth for potential disease due to vaccine virus if they are born within 14 days of their mother receiving IXCHIQ.

5.4 Syncope

Syncope (fainting) can occur in association with administration of injectable vaccines including IXCHIQ. Procedures should be in place to avoid injury from fainting.

5.5 Limitations of Vaccine Effectiveness

Vaccination with IXCHIQ may not protect all individuals.

6 ADVERSE REACTIONS

In clinical studies, the most common solicited injection site reaction (>10%) was tenderness (10.6%). The most common solicited systemic adverse reactions (>10%) were headache (31.6%), fatigue (28.5%), myalgia (23.9%), arthralgia (17.2%), fever (13.5%) and nausea (11.2%).

6.1 Clinical Trials Experience

Because clinical trials are conducted under widely varying conditions, adverse reaction rates observed in the clinical trials of a vaccine cannot be directly compared to rates in the clinical trials of another vaccine and may not reflect the rates observed in practice.

The safety of IXCHIQ was evaluated in two clinical studies [Study 1 (NCT04546724), Study 2 (NCT04786444)], both conducted in North America, in which a total of 3,490 participants 18 years of age and older received a dose of IXCHIQ.), Study 2 (NCT04786444)], both conducted in North America, in which a total of 3,490 participants 18 years of age and older received a dose of IXCHIQ.

Study 1 was a randomized, placebo-controlled, double-blinded study, in which participants were vaccinated with a single dose of IXCHIQ (n=3,082) or placebo (Phosphate Buffered Saline) (n=1,033). Study 2 was a non-placebo-controlled study where 408 participants were vaccinated with a single dose of IXCHIQ. Among the overall 4,523 participants enrolled in those studies, 54.7% were female; 80.1% were White, 14.0% Black or African American, 1.9% Asian, 0.8% American Indian or Alaska Native, 0.4% Native Hawaiian or Pacific Islander, 2.7% Other racial groups; and 17.2% were Hispanic or Latino.

In Studies 1 and 2, solicited adverse reactions, including injection site and systemic adverse reactions, were collected via electronic diary in the first 10 days post-vaccination. An electronic memory aid was distributed to each participant for the collection of safety information outside the first ten post-vaccination days until the next visit. Unsolicited adverse events, chikungunya-like adverse reactions, and serious adverse events were monitored through 6 months post-vaccination. In Study 1, hematology parameters were assessed at enrollment, 7, 28, 84 and 180 days post-vaccination in a subset of participants who were evaluated for seroresponse to vaccination (immunogenicity subset). [See Clinical Studies (14)].

Solicited Adverse Reactions

In Study 1, the median age of participants was 45 years (range 18 through 94 years); 54.7% were female and 45.3% male; 80.4% were White, 13.9% Black or African American, 1.7% Asian, 0.8% American Indian or Alaska Native, 0.4% Native Hawaiian or Pacific Islander, 2.8% Other racial groups; and 17.5% were Hispanic or Latino. IXCHIQ and placebo groups were similar with regard to demographics.

The percentage of participants in Study 1 reporting solicited local and systemic adverse reactions is shown in Table 1. The median day of onset was Day 2 for local reactions (Day 1 was the day of vaccination) and Day 5 for systemic reactions. Local and systemic adverse reactions resolved with a median duration of 2 days.

Table 1. Percentage of Participants with Solicited Local and Systemic Adverse Reactions Within 10 Days After Vaccination (Study 1§)
Category | IXCHIQ (N=3,082) % | Placebo (N=1,033) %
Solicited Injection Site Adverse Reactiona
Tenderness (any)b | 10.6 | 8.1
Tenderness (severe) | 0 | 0
Pain (any)c | 6.2 | 3.7
Pain (severe) | 0.03 | 0
Erythema/Redness (≥ 2.5 cm)d | 1.5 | 1.5
Induration (≥ 2.5 cm)d | 1.4 | 0.8
Swelling (≥ 2.5 cm)d | 0.7 | 0.8
Solicited Systemic Adverse Reactiona
Headache (any)a | 31.6 | 14.7
Headache (severe)e | 0.1 | 0.1
Fatigue (any)a | 28.5 | 12.7
Fatigue (severe)e | 0.2 | 0
Myalgia/Muscle Pain (any)a | 23.9 | 7.4
Myalgia/Muscle Pain (severe)e | 0.3 | 0
Arthralgia/Joint Pain (any)a | 17.2 | 4.9
Arthralgia/Joint Pain (severe)e | 0.3 | 0
Fever (any)f | 13.5 | 0.9
Fever (severe or worse)g | 1.4 | 0
Nausea (any)a | 11.2 | 5.6
Nausea (severe)e | 0 | 0.1
Rash (any)a | 2.3 | 0.5
Rash (severe)h | 0 | 0
Vomiting (any)a | 1.9 | 1.0
Vomiting (severe)e | 0 | 0.1
§NCT04546724
N=Number of participants
a Severity=mild, moderate, severe intensity.
b defined as mild (mild discomfort to touch), moderate (discomfort with movement), severe (significant discomfort at rest). Any potentially life threatening event (emergency room visit or hospitalization) was to be reported as severe.
c defined as mild (does not interfere with activity), moderate (repeated use of non-narcotic pain reliever > 24 hours or interferes with activity), severe (any use of narcotic pain reliever or prevents daily activity). Any potentially life threatening event (emergency room visit or hospitalization) was to be reported as severe.
d No participants had erythema, induration or swelling >10 cm
e Severe=Prevents daily activity (for fatigue, myalgia, and arthralgia); Prevents daily activity and requires medical intervention (for headache, nausea, vomiting)
f defined as temperature ≥38.0°C (100.4°F)
g defined as temperature ≥39.0°C (102.1°F)
h Severe=Macules/papules covering >30% body surface area with or without associated symptoms; limiting self-care activity of daily living.

Hematology Parameters

In Study 1, hematology parameters were assessed at 7, 28, 84 and 180 days post-vaccination in the immunogenicity subset. Percentages of study participants with abnormally low leukocyte, neutrophil and lymphocyte counts are presented by maximum grade post-vaccination in Table 2. Abnormal leukocyte, neutrophil and lymphocyte counts were more frequently observed in IXCHIQ recipients than placebo recipients. Of 186 participants with abnormal cell counts at the 7-day post-vaccination assessment, 171 (171/186, 92%) had available hematology results at the 28-day post-vaccination assessment, of which 150 (150/171, 88%) were in the normal range.

Table 2. Abnormal Hematology Results by Maximum Grade Post-vaccination (Study 1§)
Laboratory Parameter Grade | IXCHIQa (N=372) n (%) | Placeboa (N=125) n (%)
Leukocytes
Grade 1 2,500 – 3,500 cell/mm^3 | 99 (27.3) | 7 (5.8)
Grade 2 1,500 – 2,499 cell/mm^3 | 16 (4.4) | 0
Grade 3 1,000 – 1,499 cell/mm^3 | 1 (0.3) | 0
Grade 4 <1,000 cell/mm^3 | 0 | 0
Neutrophils
Grade 1 1,500 – 2,000 cell/mm^3 | 100 (27.6) | 14 (11.6)
Grade 2 1,000 – 1,499 cell/mm^3 | 41 (11.3) | 1 (0.8)
Grade 3 500 – 999 cell/mm^3 | 11 (3.0) | 0
Grade 4 < 500 cell/mm^3 | 1 (0.3) | 0
Lymphocytes
Grade 1 750 – 1,000 cell/mm^3 | 69 (19.1) | 8 (6.6)
Grade 2 500 – 749 cell/mm^3 | 15 (4.1) | 1 (0.8)
Grade 3 250 – 499 cell/mm^3 | 1 (0.3) | 0
Grade 4 <250 cell/mm^3 | 0 | 0
§ NCT04546724, immunogenicity subset
a Individuals are included only once under the highest grade. Percentages are based on the number of individuals with at least one postbaseline result.

Unsolicited Adverse Reactions

Unsolicited adverse events that occurred within 28 days following vaccination were reported in 21.8% of 3,082 participants who received IXCHIQ versus 13.3% of 1,033 participants who received placebo. Chills was reported by 1.8% of IXCHIQ recipients and 0.2% of placebo recipients; diarrhea was reported by 1.4% of IXCHIQ recipients and 0.4% of placebo recipients; back pain was reported by 1.1% of IXCHIQ recipients and 0.6% of placebo recipients, lymphadenopathy was reported by 0.9% of IXCHIQ recipients and 0% of placebo recipients. Chills, diarrhea, back pain, and lymphadenopathy are likely related to vaccination. There were no other notable patterns or numerical imbalances between treatment groups for specific categories of unsolicited adverse events that would suggest a causal relationship to IXCHIQ.

Serious Adverse Events

Among 3,490 IXCHIQ recipients, two (both from Study 1) reported serious adverse reactions. One IXCHIQ recipient reported myalgia and one reported atrial fibrillation and hypovolemic hyponatremia. These adverse reactions are further described under the subheading Chikungunya-Like Adverse Reactions.

Chikungunya-Like Adverse Reactions

Study 1, participants were monitored for a cluster of symptoms consistent with chikungunya. Chikungunya-like adverse reactions were defined as fever (38 °C / 100.4 °F) and one or more of any of the following: arthralgia or arthritis, myalgia, headache, back pain, rash, lymphadenopathy, or certain neurological, cardiac or ocular symptoms that occurred with an onset within 30 days after vaccination. Severe chikungunya-like adverse reactions were those that prevented daily activity and/or required medical intervention.

Among Study 1 participants, 361 (11.7%) in the IXCHIQ group (n= 3,082) reported chikungunya-like adverse reactions, including 48 participants (1.6%) who reported severe chikungunya-like adverse reactions. Six (0.6%) participants in the placebo group (n= 1,033) reported chikungunya-like adverse reactions, none of which were severe. The frequencies of chikungunya-like symptoms among the IXCHIQ recipients with chikungunya-like adverse reactions are presented in Table 3.

Table 3. Frequency of Chikungunya-Like Symptoms Among Participants With Chikungunya-Like Adverse Reactions (Study 1§)
Chikungunya-Like Symptom Chikungunya-Like Symptom (severe) | IXCHIQ (N=361) % (n)
Pyrexia (any) Pyrexia (severe) | 100 (361) 10.8 (39)
Headache (any) Headache (severe) | 77.6 (280) 0.3 (1)
Fatigue (any) Fatigue (severe) | 73.1 (264) 0.6 (2)
Myalgia (any) Myalgia (severe) | 59.6 (215) 0.8 (3)
Arthralgia (any) Arthralgia (severe) | 44.0 (159) 1.4 (5)
Chills (any)a | 8.0 (29)
Rash (any)a | 6.1 (22)
Back pain (any) Back pain (severe) | 3.6 (13) 0.3 (1)
Lymphadenopathy (any)a | 2.5 (9)
Dizziness (any)a | 1.7 (6)
Pain (any)a | 1.1 (4)
Paresthesia (any)a | 0.8 (3)
Hyperhidrosis (any)a | 0.6 (2)
Edema peripheral (any)a | 0.6 (2)
Asthenia (any)a | 0.3 (1)
Ataxia (any)a | 0.3 (1)
Atrial fibrillation (any) Atrial fibrillation (severe) | 0.3 (1) 0.3 (1)
Feeling abnormal (any)a | 0.3 (1)
Hypoesthesia (any)a | 0.3 (1)
Influenza like illness (any)a | 0.3 (1)
Neuropathy peripheral (any)a | 0.3 (1)
Rash erythematous (any)a | 0.3 (1)
Syncope (any)a | 0.3 (1)
§NCT04546724
N=Number of participants with chikungunya-like adverse reactions; n=number of participants with chikungunya-like symptom.
a No severe chikungunya-like symptoms reported.

The median onset of chikungunya-like adverse reactions in IXCHIQ recipients was 4.0 days (range 1 to 11 days) after vaccination. The median duration of chikungunya-like adverse reactions in IXCHIQ recipients was 4.0 days (range 1 day to at least 6 months) after vaccination.

Fourteen IXCHIQ recipients had prolonged (duration at least 30 days) chikungunya-like adverse reactions (median duration 94 days, range 30 days to at least 6 months). Prolonged fatigue, headache and myalgia were each reported by three participants. Prolonged arthralgia was reported by five participants, including a 46-year-old male who reported severe arthralgia and back pain that lasted for at least 51 days after vaccination and a 50-year-old female who reported polyarthralgia and nodular swelling of joints in fingers and foot that lasted for at least 6 months after vaccination.

Two IXCHIQ recipients experienced serious chikungunya-like adverse reactions. A 58-year-old female with a history of fibromyalgia experienced severe myalgia, mild arthralgia, tachycardia and tachypnea, with onset of symptoms 1 to 2 days after vaccination, was hospitalized on Days 4 through 10 post-vaccination, and fully recovered, with myalgia resolving after 30 days. A 66-year-old male experienced severe fever on Days 5 through 11 post-vaccination, was hospitalized on Days 10 through 12 post-vaccination and found to have atrial fibrillation, increased troponin, increased brain natriuretic peptide and hypovolemic hyponatremia, and fully recovered. This study participant was included in a subset of participants assessed for vaccine viremia 7 days after vaccination and was found to be viremic.

8 USE IN SPECIFIC POPULATIONS

8.1 Pregnancy

Pregnancy Exposure Registry

There is a pregnancy exposure registry that monitors pregnancy outcomes in individuals exposed to IXCHIQ during pregnancy. Individuals who receive IXCHIQ during pregnancy are encouraged to contact directly, or have their healthcare professional contact, OXON Epidemiology at 1-855-417-6214 to enroll in or obtain information about the registry.

Risk Summary

All pregnancies have a risk of birth defect, loss, or other adverse outcomes. In the US general population, the estimated background risk of major birth defects and miscarriage in clinically recognized pregnancies is 2% to 4% and 15% to 20%, respectively.

There are no adequate and well-controlled studies of IXCHIQ in pregnant individuals, and human data available from clinical trials with IXCHIQ are insufficient to establish the presence or absence of vaccine-associated risk during pregnancy.

A developmental study was conducted in female rats. Animals were administered a single human dose of IXCHIQ on 2 occasions, once prior to mating and once during gestation. This study revealed no evidence of harm to the fetus and no adverse effects on post-natal development due to the vaccine [See Animal Data].

Clinical Considerations

Disease-associated maternal and/or embryo/fetal risk

Vertical transmission of wild-type CHIKV to neonates from pregnant individuals with viremia at delivery is common and can cause severe, potentially fatal CHIKV disease in neonates, with neurologic (e.g., encephalopathy, intracranial hemorrhage) and myocardial manifestations. Vertical transmission of wild-type CHIKV and fetal death attributable to CHIKV in the context of antepartum infection has been reported to occur infrequently [See Data].

Fetal/neonatal adverse reactions

Vaccine viremia occurred in the first week following administration of a vaccine containing the same attenuated CHIKV as in IXCHIQ [See Description (11)], with resolution of viremia by 14 days after vaccination [See Clinical Pharmacology (12.2)]. It is not known if the vaccine virus can be transmitted from a pregnant individual to the fetus or neonate and cause fetal or neonatal adverse reactions.

Decisions to administer IXCHIQ during pregnancy should take into consideration the individual’s risk of exposure to wild-type CHIKV, gestational age, and risks to the fetus or neonate from vertical transmission of wild-type CHIKV.

Closely monitor neonates for 7 days after birth for potential disease due to vaccine virus if they are born within 14 days of their mother receiving IXCHIQ.

Data

Human data

In a prospective study conducted during an outbreak of CHIKV, vertical transmission of wild-type CHIKV to neonates from infected pregnant individuals was assessed. Among pregnant individuals infected prepartum (N=22) or intrapartum (N=39) (symptomatic between day -7 and day -3, or day -2 and day 2 around delivery, respectively and concomitant positive serum CHIKV RT-PCR or IgM serology when PCR not available) vertical transmission occurred in 19, all with an intrapartum infection (vertical transmission rate of 48.7% for intrapartum infections). Severe CHIKV disease was reported in 52.6% (10/19) of these infected neonates. Among 678 pregnant individuals infected antepartum (symptomatic between conception and the week preceding labor and positive serum CHIKV RT-PCR or IgM serology) fetal death attributed to CHIKV occurred in three (0.4%). In these three cases, onset of CHIKV symptoms in the pregnant individual ranged from approximately 12 weeks to 15 weeks gestation and the fetal death occurred approximately two weeks later. For these fetal deaths, amniotic fluid before fetal death was CHIKV RT-PCR positive. CHIKV RNA was detected in the placenta and in the fetal brain for two.^1

Animal Data

In a pre- and post-natal developmental study with an embryo-fetal development toxicity phase conducted in female rats, a full human dose of IXCHIQ (0.5 mL) was administered by intramuscular injection on 2 occasions to determine the effect on female fertility, reproductive performance, and pre- and post-natal development: 14 days prior to mating, and on gestation day 6. No vaccine related adverse effects on fetal development, reproductive performance, and pre- and post-natal development were reported.

8.2 Lactation

Risk Summary

Human data are not available to assess the impact of IXCHIQ on milk production, its presence in breast milk, or its effects on the breastfed child. The developmental and health benefits of breastfeeding should be considered along with the mother's clinical need for IXCHIQ and any potential adverse effects on the breastfed child from IXCHIQ or from the underlying maternal condition. For preventive vaccines, the underlying condition is susceptibility to disease prevented by the vaccine.

Clinical Considerations

Fetal/neonatal adverse reactions

Vaccine viremia occurs after vaccination. In a clinical trial, vaccine virus was not detectable at 14 days after vaccination [See Clinical Pharmacology (12.2)]. The potential for transmission of the vaccine virus from mother to infant through breastmilk is unknown.

Data

Animal Data

One developmental toxicity study was performed in which female rats were administered IXCHIQ at a single dose of up to 300 fold excess relative to the projected human dose (on a mg/kg basis). IXCHIQ-specific antibodies were detected in the milk of vaccinated female rats from day 5 of lactation.

8.4 Pediatric Use

The safety and effectiveness of IXCHIQ in individuals younger than 18 years of age have not been established.

8.5 Geriatric Use

Of the total number of participants in clinical studies of IXCHIQ 9.6% (n=346) were 65 years of age and older, while 1.6% (n=59) were 75 and older. [See Adverse Reactions (6.1) and Clinical Studies (14)]. In Study 1, no overall difference in effectiveness was observed between participants 65 years of age and older and younger participants. Study 1 did not include sufficient numbers of participants 65 years of age and older to determine if there was an overall difference in safety between these participants and younger participants.

11 DESCRIPTION

IXCHIQ (Chikungunya Vaccine, Live) is a solution for intramuscular injection. IXCHIQ is supplied as a vial of sterile, Lyophilized Antigen Component, Live, and a syringe of Sterile Water Diluent Component. The Lyophilized Antigen Component, Live, is reconstituted at the time of use with the accompanying Sterile Water Diluent Component to form IXCHIQ. The Lyophilized Antigen Component, Live, is a white to slightly yellowish powder. After reconstitution, IXCHIQ is a clear colorless to slightly yellowish solution.

IXCHIQ contains live, attenuated chikungunya virus (generated by reverse genetics from La Réunion strain LR-CHIKV clone LR2006 OPY1). The attenuated virus has a deletion in non-structural protein 3, which encodes a component of the viral replicase complex, and replicates less efficiently than the wild-type CHIKV. The vaccine virus is propagated in Vero cells (a continuous line of monkey kidney cells) in media containing amino acids, vitamins, minerals and fetal bovine serum. The viral harvests are pooled, clarified and concentrated. The virus is purified by chromatography and ultracentrifugation, mixed with formulation buffer and lyophilized.

After reconstitution, each approximately 0.5-mL dose contains not less than 3.0 log10 TCID50 (Tissue Culture Infectious Dose 50%) of live, attenuated chikungunya virus. Each dose also contains 0.05 mg recombinant human albumin, 25 mg sucrose, 2.5 mg D-sorbitol, 0.75 mg L-methionine, 0.51 mg magnesium chloride hexahydrate, 3.68 mg trisodium citrate di-hydrate, 0.313 mg di-potassium hydrogen phosphate, and 0.098 mg potassium di-hydrogen phosphate. Each dose may contain residual amounts of Vero cell proteins (less than 5 ng/dose), Vero cell DNA (less than 10 pg/dose), bovine serum albumin (less than 500 pg/dose) and protamine sulphate (less than 1 mcg/dose), from the manufacturing process.

IXCHIQ does not contain a preservative.

The stoppers of the syringes containing Sterile Water Diluent Component and the stoppers of the vials containing Lyophilized Antigen Component, Live, are not made with natural rubber latex.

12 CLINICAL PHARMACOLOGY

12.1 Mechanism of Action

The exact mechanism of protection has not been determined. IXCHIQ elicits CHIKV-specific immune responses.

12.2 Pharmacokinetics

Viremia and urinary shedding

Quantitative reverse transcription-polymerase chain reaction (qRT-PCR) was used to assess vaccine viremia in plasma and urinary shedding after vaccination on Days 1 (day of vaccination), 4, 8 and 15 in one Phase 1 study (NCT03382964). Participants were vaccinated with a single dose of one of three dose levels [low (3.5 log10 TCID50/dose), medium (4.5 log10 TCID50/dose), and high (5.5 log10 TCID50/dose)] of a formulation containing the same attenuated CHIKV used in IXCHIQ. The amount of attenuated CHIKV in each medium dose was equivalent to the maximum amount in a dose of IXCHIQ. Viremia was not detected in any participant in any study arm on Day 1. The highest proportion of viremic participants was observed at the Day 4 time point (81%, 90%, and 95% in the low, medium, and high dose groups, respectively, Table 4). Viremia had resolved in all participants by the Day 15 time point, including those who received the high dose formulation. The vaccine virus was detected in the urine of one participant in the low dose group on Day 8.

Table 4. Plasma Viremia on Days 4, 8 and 15 in participants vaccinated with a formulation containing attenuated CHIKV (Study NCT03382964)
Visit |  | Attenuated CHIKV Formulation
Visit |  | Low^1 Dose (N=31) | Medium^2 Dose (N=30) | High^3 Dose (N=59)
Day 4 | Participants with quantifiable viremia, n/N (%) | 25 / 31 (81%) | 27 / 30 (90%) | 56 / 59 (95%)
Day 4 | Mean plasma viremia (GCE§/mL) | 73,601 | 89,354 | 229,224
Day 8 | Participants with quantifiable viremia, n/N (%) | 6 / 31 (19%) | 5 / 30 (17%) | 4 / 59 (7%)
Day 8 | Mean plasma viremia (GCE§/mL) | 8814 | 15,725 | 27,028
Day 15 | Participants with quantifiable viremia, n/N (%) | 0 / 31 (0%) | 0 / 30 (0%) | 0 / 59 (0%)
Day 15 | Mean plasma viremia (GCE§/mL) | N/A* | N/A* | N/A*
§ GCE = genome copy equivalent; * N/A = not applicable
Dose TCID50: ^1low (3.5 log10 TCID50/dose), ^2medium (4.5 log10 TCID50/dose), ^3high (5.5 log10 TCID50/dose)]

13 NONCLINICAL TOXICOLOGY

13.1 Carcinogenesis, Mutagenesis, Impairment of Fertility

IXCHIQ has not been evaluated for carcinogenic or mutagenic potential or impairment of male fertility. In a developmental toxicity study conducted in rats, there were no vaccine-related effects on female fertility [See Use in Specific Populations (8.1)].

13.2 Animal Toxicology and/or Pharmacology

A passive transfer study was performed in non-human primates (NHPs) using human anti-CHIKV immune sera collected from a Phase 1 study (NCT03382964). In the Phase 1 study, participants received a single dose of a vaccine formulation containing the same attenuated CHIKV used in IXCHIQ. Sera obtained between Days 14 and 180 after vaccination were pooled to generate 8 serum pools representing varying anti-CHIKV neutralizing antibody titers. In the passive transfer study, 40 CHIKV-naïve cynomolgus macaques (M. fascicularis) were administered human anti-CHIKV immune sera from the 8 serum pools (n=5 per group) and 6 CHIKV-naïve cynomolgus macaques were administered non-immune control sera by intravenous injection. One day after the transfers, serum samples were obtained from the macaques to determine pre-challenge anti-CHIKV neutralizing antibody titers by μPRNT50 assay. Animals were challenged with 100 times the 50% animal infectious dose of wild-type CHIKV strain La Réunion 2006-OPY1, corresponding to 7,000–10,000 Plaque Forming Units. Animal monitoring included assessment of wild-type CHIKV-induced viremia by RT-qPCR and body temperature through 14 and 28 days after challenge, respectively. None of the animals receiving post-vaccination serum pools developed fever after the challenge. Fever and viremia within 7 days post-challenge were detected in all 6 macaques receiving non-immune human sera. Data from the NHP study were analyzed by logistic regression and a μPRNT50 titer of ≥150 was determined to be reasonably likely to predict clinical benefit in the Phase 3 study.

14 CLINICAL STUDIES

IXCHIQ effectiveness against disease caused by CHIKV was based on an evaluation of seroresponse defined as an anti-CHIKV neutralizing antibody level above a threshold (PRNT50 titer 150). This threshold was derived from a non-human primate model [See Nonclinical Toxicology (13.2)].The seroresponse rate 28 days after a single dose of IXCHIQ is presented in Table 5.

Table 5. Seroresponse Rates 28 Days Post-Vaccination as Determined by µPRNT Assay, in Study 1 (PP Population)
IXCHIQ | Placebo
N=266 | N=96
% (n) [95%CI] | % [95%CI]
98.9 (263) [96.7, 99.8]* | 0 [0.0, 3.8]
Abbreviations: CI=confidence interval; µPRNT=micro plaque reduction neutralization test; PP=per-protocol (population). *Success criterion: lower bound of the 95% confidence interval for seroresponse rate >70%.

The seroresponse rate 180 days after a single dose of IXCHIQ was 96.3% (95% CI: 93.1, 98.3).

15 REFERENCES

1. Gérardin P, Barau G, Michault A, Bintner M, Randrianaivo H, Choker G, et al. Multidisciplinary prospective study of mother-to-child chikungunya virus infections on the island of La Réunion. PLoS Med. 2008;5(3):0413–2

16 HOW SUPPLIED/STORAGE AND HANDLING

16.1 How Supplied

IXCHIQ is supplied in a carton (NDC 42515-003-01) containing:

- one single-dose vial of Lyophilized Antigen Component, Live (NDC 42515-004-01)
- one prefilled ungraduated syringe of Sterile Water Diluent Component (NDC 42515-005-01) (packaged without needles).

16.2 Storage and Handling

Store vial of Lyophilized Antigen Component, Live, and syringe of Sterile Water Diluent Component in a refrigerator at 2°C to 8°C (35°F to 46°F). Store in the original carton to protect from light. DO NOT FREEZE.

17 PATIENT COUNSELING INFORMATION

Advise the vaccine recipient to read the FDA-approved patient labeling (Patient Information).

Question the vaccine recipient about reactions to previous vaccines.

Inform the vaccine recipient of the benefits and risks of IXCHIQ, including:

- the potential for severe or prolonged chikungunya-like adverse reactions [See Warnings and Precautions (5.2)], and
- the potential for vertical transmission of vaccine virus from pregnant individuals and potential fetal/neonatal adverse reactions [See Warnings and Precautions (5.3)].

Advise the recipient that IXCHIQ may not protect everyone who gets the vaccine and that personal precautions should be taken to reduce exposure to mosquito bites (e.g., adequate clothing, use of repellents, mosquito nets).

There is a pregnancy exposure registry for IXCHIQ. Encourage individuals exposed to IXCHIQ around the time of conception or during pregnancy to register by calling 1-855-417-6214 or by visiting www.valneva-oxon.com/IXCHIQPregnancyRegistry [See Use in Specific Populations (8.1)].

Advise vaccine recipient to report any adverse reactions to their healthcare provider or to the Vaccine Adverse Event Reporting System (VAERS) at 1-800-822-7967 and www.vaers.hhs.gov.

Manufactured by:
Valneva Scotland Ltd.Oakbank Park Road, EH53 0TG, Livingston, UKT: +44.1506.446.600F: +44.1506.446.601www.valneva.com

Distributed by:
Valneva USA Inc.
Bethesda, MD 20814
USA

Patient Information

IXCHIQ (pronounced “ǐks-chēk”)

Generic name: chikungunya vaccine, live

Read this information about IXCHIQ before you are vaccinated. If you have any questions about IXCHIQ after reading this leaflet, ask your healthcare provider. This leaflet does not take the place of talking with your healthcare professional about IXCHIQ. Only your healthcare provider can decide if IXCHIQ is right for you.

What is IXCHIQ?

IXCHIQ is a vaccine for use in individuals 18 years of age and older to help protect against chikungunya virus disease.

- You should still protect yourself from mosquito bites even if you have received the IXCHIQ vaccine.
- IXCHIQ may not fully protect everyone who gets the vaccine.
- IXCHIQ does not protect against other diseases transmitted by mosquitoes.

Who should not get IXCHIQ?

You should not get IXCHIQ if you:

- have a weakened immune system due to certain conditions or therapy.
- have ever had a severe allergic reaction to any of the ingredients in the vaccine. A list of ingredients can be found at the end of this leaflet.

IXCHIQ is not approved for use in individuals below the age of 18 years.

What should I tell my healthcare professional before I am vaccinated with IXCHIQ?

It is very important to tell your healthcare provider if you:

- have had an allergic reaction to any ingredient of IXCHIQ.
- have a bleeding disorder or are on a blood thinner.
- have a weakened immune system due to a condition or therapy.
- are or may be pregnant, or are breast feeding.
- currently have any illness with a fever of more than 38.0 °C (100.4 °F).
- take any medicines, even those you can buy over the counter.

How is IXCHIQ given?

IXCHIQ is given as an injection into the muscle.

What are the risks of IXCHIQ?

IXCHIQ commonly causes symptoms similar to those experienced by people who have chikungunya disease, e.g., fever, headache, fatigue, muscle pain and joint pain. In some people who receive IXCHIQ, these symptoms may prevent daily activity, require medical intervention including hospitalization, and last for weeks or months.

In some people IXCHIQ causes a decrease in the numbers of white blood cells. This usually occurs within the first week following vaccination. In most people, the numbers of white blood cells return to normal on their own within one month.

The most common side effects of IXCHIQ are headache, fatigue, muscle pain, joint pain, fever, tenderness at the injection site and nausea.

These are not all of the possible side effects of IXCHIQ. You can ask your healthcare provider about other side effects that have been reported.

Contact your healthcare provider right away if you get any symptoms that concern you after receiving IXCHIQ.

Tell your healthcare provider if you have any of the following problems after receiving IXCHIQ because these may be signs of an allergic reaction:

- difficulty breathing
- hoarseness or wheezing
- hives
- dizziness, weakness or fast heart beat

You may report side effects to the Vaccine Adverse Event Reporting System (VAERS) at 1-800-822-7967 or https://vaers.hhs.gov.

What are the ingredients of IXCHIQ?

IXCHIQ contains weakened live chikungunya virus (CHIKV), recombinant human albumin, sucrose, D-sorbitol, L-methionine and salts. IXCHIQ may contain trace amounts of bovine serum albumin, Vero cell protein, Vero cell DNA and protamine sulphate.

What else should I know about IXCHIQ?

This leaflet is a summary of information about IXCHIQ. If you would like more information, please talk to your healthcare provider.

11/2023

License Holder:
Valneva Austria GmbH
Campus Vienna Biocenter 31030 Vienna, Austria

Manufactured byValneva Scotland Ltd.
Oakbank Park Rd,
Livingston EH53 0TG, United Kingdom

Distributed by:
Valneva USA Inc.Bethesda, MD 20814USA

Principal display panel

Text from principal display panel

NDC 42515-003-01

Rx only
Licence number: 1909
Contains no preservatives
No US standard of potency

chikungunya vaccine, live
IXCHIQ
Solution for Intramuscular Injection

For 18 years of age and older.
Content:

- 1 single dose vial of lyophilized vaccine
- 1 single dose prefilled syringe of diluent